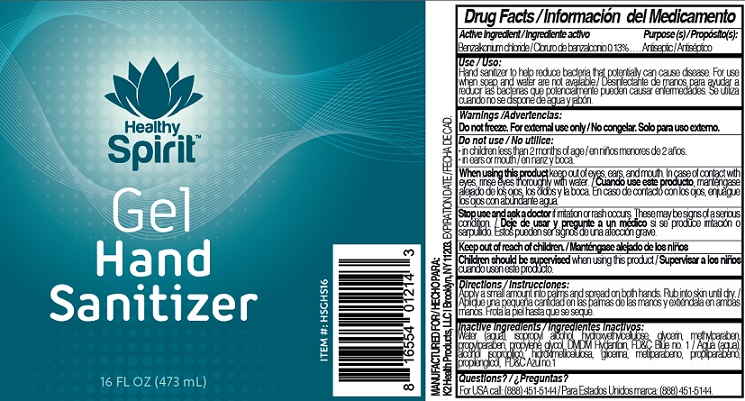 DRUG LABEL: Healthy Spirit
NDC: 73745-001 | Form: GEL
Manufacturer: K2 HEALTH PRODUCTS LLC
Category: otc | Type: HUMAN OTC DRUG LABEL
Date: 20200511

ACTIVE INGREDIENTS: BENZALKONIUM CHLORIDE 0.13 g/100 mL
INACTIVE INGREDIENTS: WATER; ISOPROPYL ALCOHOL; HYDROXYETHYL CELLULOSE, UNSPECIFIED; GLYCERIN; METHYLPARABEN; PROPYLPARABEN; PROPYLENE GLYCOL; DMDM HYDANTOIN; FD&C BLUE NO. 1

Active Ingredient

Benzalkonium chloride 0.13%

Purpose

Antiseptic

Use

Hand Sanitizer to help reduce bacteria that potentially can cause disease. For use when soap and water are not available.

Warnings

Do not freeze. For external use only.

Do not use

- in children less than 2 months of age
- in ears or mouth

When using this product keep out of eyes, ears, and mouth. In case of contact with eyes, rinse eyes thoroughly with water.

Stop use and ask a doctor if irritation or rash occurs. These may be signs of a serious condition.

Keep out of reach of children.

Children should be supervised when using this product.

Directions

Apply a small amount into palms and spread on both hands. Rub into skin until dry.

Inactive ingredients

Isopropyl alcohol, Hydroxyethyl celleulose, glycerin, methylparaben, propylparaben, Propylene glycol, Dmdm hydantoin, FD&C Blue no 1